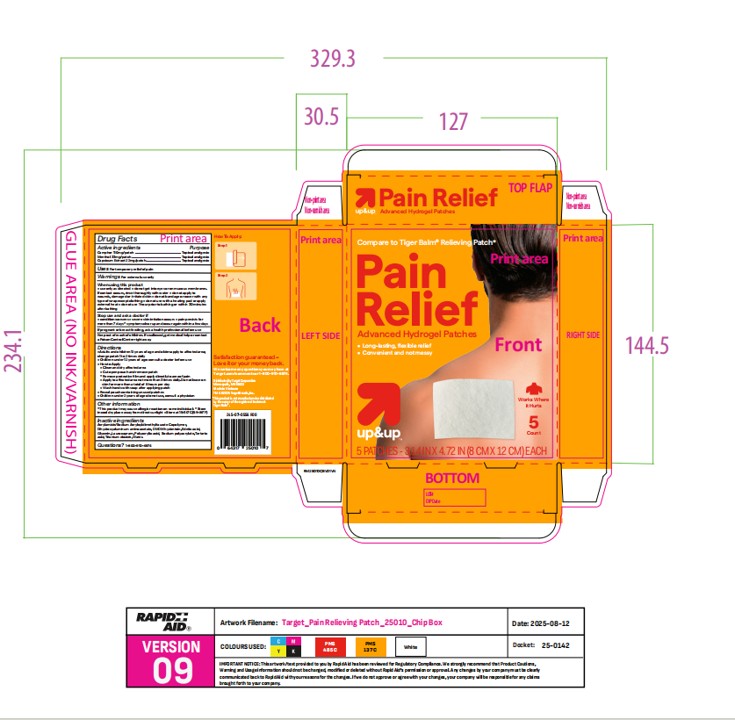 DRUG LABEL: Up up
NDC: 82442-745 | Form: PATCH
Manufacturer: Target Corporation
Category: otc | Type: HUMAN OTC DRUG LABEL
Date: 20251120

ACTIVE INGREDIENTS: CAPSICUM 22 mg/1000 mg; CAMPHOR (SYNTHETIC) 110 mg/1000 mg; LEVOMENTHOL 33 mg/1000 mg
INACTIVE INGREDIENTS: EDETIC ACID; DIHYDROXYALUMINUM AMINOACETATE ANHYDROUS; GLYCERIN; LAUROCAPRAM; POLYACRYLIC ACID (800000 MW); WATER; DMDM HYDANTOIN; SODIUM POLYACRYLATE (8000 MW); ACRYLAMIDE/SODIUM ACRYLOYLDIMETHYLTAURATE COPOLYMER (120000 MPA.S AT 1%); TARTARIC ACID; TITANIUM DIOXIDE

Purpose

Topical analgesic

Active Ingredient(s)

Camphor 110mg +Menthol 33mg + Capsicum Extract 22mg

Use

For temporary relief of pain

Warnings

For external use only.

When using this product:

Use only as directed

do not get into eyes or on mucous membranes. If contact occurs, rinse thoroughly with water

do not apply to wounds, damaged or irritated skin

do not bandage or cover with any type of wrap except clothing

do not use with a heating pad or apply external heat

do not use 1 hour prior to bathing or within 30 minutes after bathing

Stop use and ask a doctor if:

Condition worsens,

Severe skin irritation occurs

Pain persist for more than 7 days

Symptoms clear up and occur again within a few days.

If pregnant or breast feeding, ask a health professional before use.

Keep out of reach of children. If swallowed, get medical help or contact a Poison Control Center right away.

Directions

Adults and children 12 years of age and older:apply to affected area; change patch 1 to 2 times daily

Children under 12 years of age: consult a doctor before use

How to Apply

Clean and dry affected area

Cut open pouch and remove patch

Remove protective film and apply directly to area of pain

Apply to affected area not more than 3 times daily. Do not leave on skin for more than a total of 8 hours per day

Wash hands with soap after applying patch

Reseal pouch containing unused patches

Children under 2 years of age: do not use, consult a physician

Other information

This product may cause allergic reaction on some individuals

Store in cool dry place away from direct sunlight

Store at 15-30°C (59-86°F)

Inactive ingredients

Acrylamide/Sodium Acryloyldimethyltaurate Copolymer, Dihydroxyaluminum aminoacetate, DMDM hydantoin, Edetic acid, Glycerin, Laurocapram, Polyacrylic acid, Sodium polyacrylate, Tartaric acid, Titanium dioxide, Water